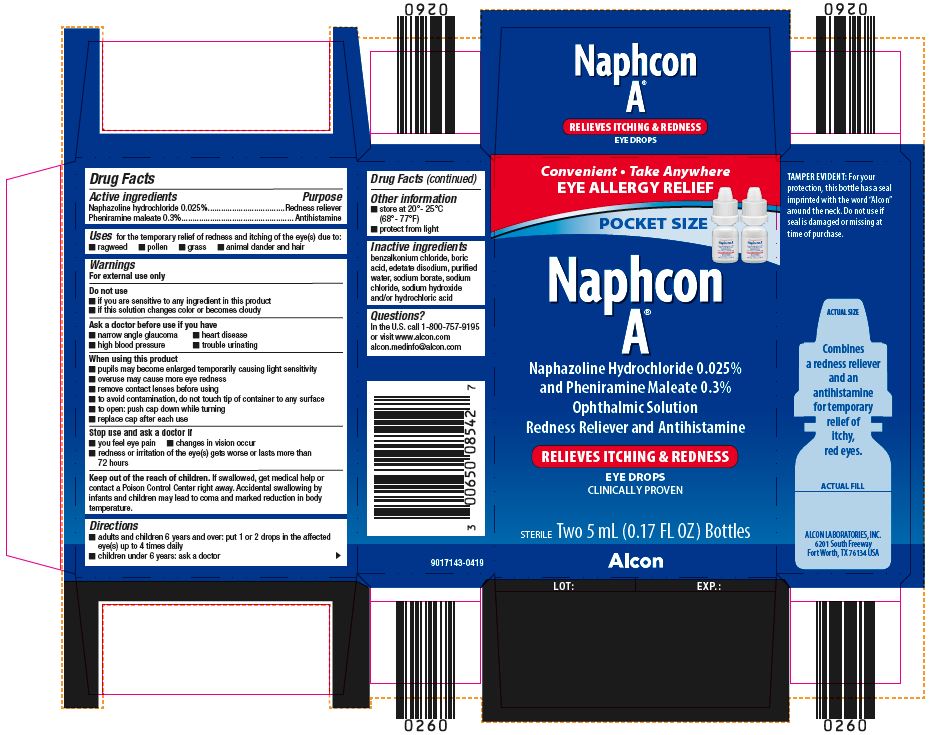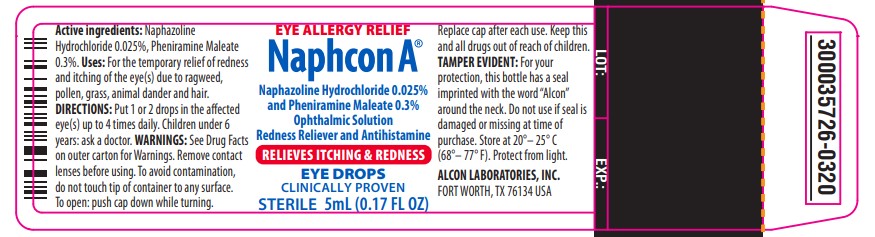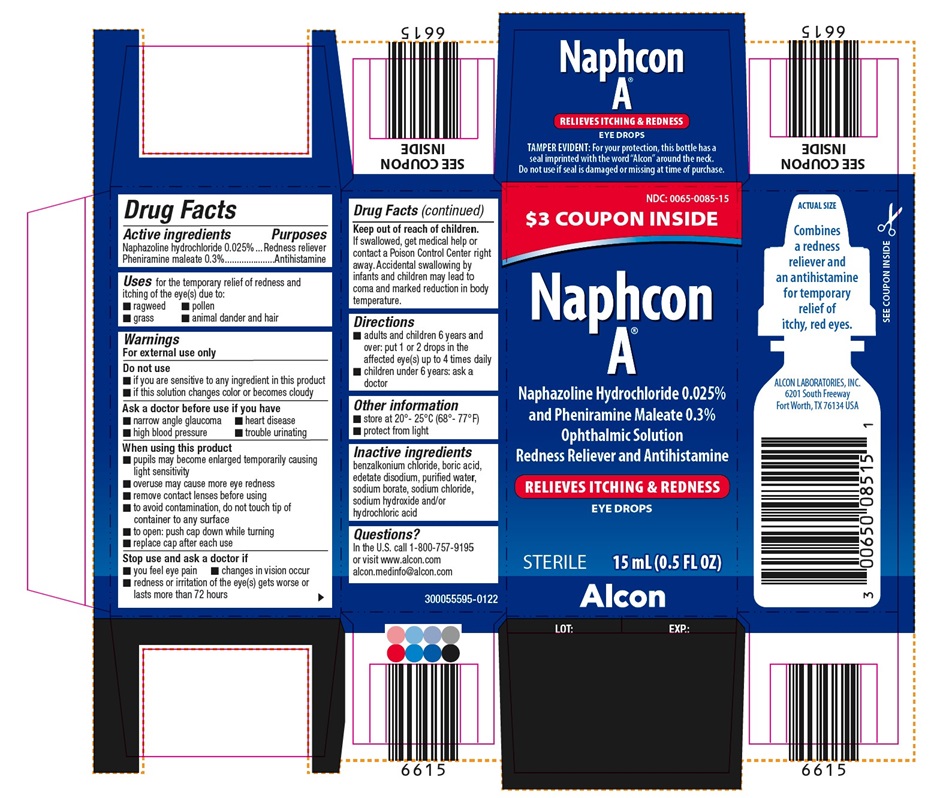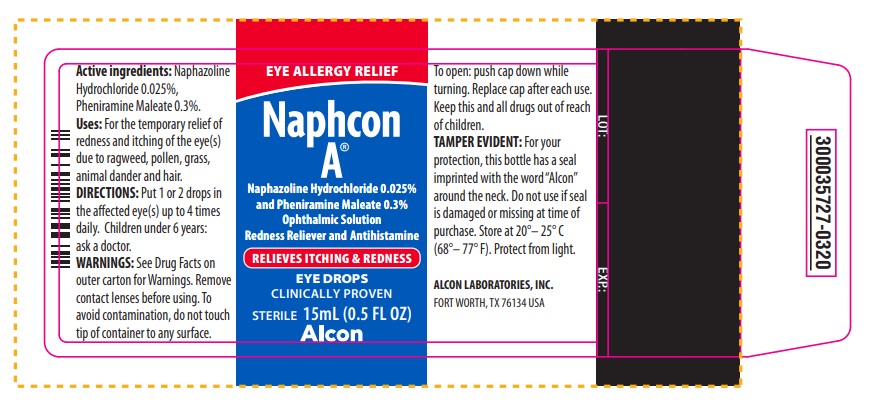 DRUG LABEL: Naphcon A 
NDC: 0065-0085 | Form: SOLUTION/ DROPS
Manufacturer: Alcon Laboratories, Inc.
Category: otc | Type: HUMAN OTC DRUG LABEL
Date: 20240327

ACTIVE INGREDIENTS: Naphazoline Hydrochloride 0.25 mg/1 mL; Pheniramine Maleate 3 mg/1 mL
INACTIVE INGREDIENTS: Benzalkonium Chloride; Boric Acid; Edetate Disodium; Water; Sodium Borate; Sodium Chloride; Sodium Hydroxide; Hydrochloric Acid

Drug Facts

ACTIVE INGREDIENT

Active ingredients | Purpose
Naphazoline hydrochloride 0.025% | Redness reliever
Pheniramine maleate 0.3% | Antihistamine

Uses

for the temporary relief of redness and itching of the eye(s) due to:

- ragweed
- pollen
- grass
- animal dander and hair

Warnings

For external use only

Do not use

- if you are sensitive to any ingredient in this product
- if this solution changes color or becomes cloudy

Ask a doctor before use if you have

- narrow angle glaucoma
- heart disease
- high blood pressure
- trouble urinating

When using this product

- pupils may become enlarged temporarily causing light sensitivity
- overuse may cause more eye redness
- remove contact lenses before using
- to avoid contamination, do not touch tip of container to any surface
- replace cap after each use

Stop use and ask a doctor if

- you feel eye pain
- changes in vision occur
- redness or irritation of the eye(s) gets worse or lasts more than 72 hours

Keep out of the reach of children.

If swallowed, get medical help or contact a Poison Control Center right away. Accidental swallowing by infants and children may lead to coma and marked reduction in body temperature.

Directions

- adults and children 6 years and over: put 1 or 2 drops in the affected eye(s) up to 4 times daily
- children under 6 years: ask a doctor

Other information

- store at 20°-25°C (68°-77°F)
- protect from light

Inactive ingredients

benzalkonium chloride, boric acid, edetate disodium, purified water, sodium borate, sodium chloride, sodium hydroxide and/or hydrochloric acid

Questions?

In the U.S. call 1-800-757-9195 or visit www.alcon.com

PRINCIPAL DISPLAY PANEL

$3 Coupon Inside
NAPHCON A®
Naphazoline Hydrochloride 0.025% and Pheniramine Maleate 0.3%
Ophthalmic Solution
Redness Reliever and Antihistamine
RELIEVES ITCHING & REDNESS
EYE DROPS
STERILE 15 mL (0.5 FL OZ)
TAMPER EVIDENT: For your protection, this bottle has a seal imprinted with the word “Alcon” around the neck. Do not use if seal is damaged or missing at time of purchase.
Actual Size
Combines a redness reliever and an antihistamine for the temporary relief of itchy, red eyes.
SEE COUPON INSIDE
ALCON LABORATORIES, INC.
6201 South Freeway
Fort Worth, TX 76134 USA
Alcon
LOT:
EXP.:
300055595-0122

EYE ALLERGY RELIEF
NAPHCON A®
Naphazoline Hydrochloride 0.025% and Pheniramine Maleate 0.3%
Ophthalmic Solution
Redness Reliever and Antihistamine
RELIEVES ITCHING & REDNESS
EYE DROPS
CLINICALLY PROVEN
STERILE 15 mL (0.5 FL OZ)
Alcon
Active ingredients: Naphazoline
Active ingredients: Naphazoline Hydrochloride 0.025%, Pheniramine Maleate 0.3%.
Uses: For the temporary relief of redness and itching of the eye(s) due to ragweed, pollen, grass, animal dander and hair.
DIRECTIONS: Put 1 or 2 drops in the affected eye(s) up to 4 times daily. Children under 6 years: ask a doctor.
WARNINGS: See Drug Facts on outer carton for Warnings. Remove contact lenses before using. To avoid contamination, do not touch tip of container to any surface.
To open: push cap down while turning. Replace cap after each use.
Keep this and all drugs out of reach of children.
TAMPER EVIDENT: For your protection, this bottle has a seal imprinted with the word “Alcon” around the neck. Do not use if seal is damaged or missing at time of purchase. Store at 20° - 25°C (68° - 77°F). Protect from light.
ALCON LABORATORIES, INC.
FORT WORTH, TX 76134 USA
LOT: EXP:
300035727-0320

PRINCIPAL DISPLAY PANEL

Convenient • Take Anywhere
EYE ALLERGY RELIEF
POCKET SIZE
NAPHCON A®
Naphazoline Hydrochloride 0.025% and Pheniramine Maleate 0.3%
Ophthalmic Solution
Redness Reliever and Antihistamine
Relieves Itching & Redness
EYE DROPS
CLINICALLY PROVEN
STERILE Two 5 mL (0.17 FL OZ) Bottles
TAMPER EVIDENT: For your protection, this bottle has a seal imprinted with the word “Alcon” around the neck. Do not use if seal is damaged or missing at time of purchase.
ACTUAL SIZE
Combines a redness reliever and an antihistamine for the temporary relief of itchy, red eyes.
ACTUAL FILL
ALCON LABORATORIES, INC.
6201 South Freeway
Fort Worth, TX 76134
ALCON
LOT:
EXP.:
9017143-0419

PRINCIPAL DISPLAY PANEL

EYE ALLERGY RELIEF
NAPHCON A®
Naphazoline Hydrochloride 0.025% and Pheniramine Maleate 0.3% Ophthalmic Solution
Redness Reliever and Antihistamine
RELIEVES ITCHING & REDNESS
EYE DROPS
CLINICALLY PROVEN
STERILE 5mL (0.17 FL OZ)
Active ingredients: Naphazoline Hydrochloride 0.025%, Pheniramine Maleate 0.3%.
Uses: For the temporary relief of redness and itching of the eye(s) due to ragweed, pollen, grass, animal dander and hair.
DIRECTIONS: Put 1 or 2 drops in the affected eye(s) up to 4 times daily. Children under 6 years: ask a doctor.
WARNINGS: See Drug Facts on outer carton for Warnings. Remove contact lenses before using. To avoid contamination, do not touch tip of container to any surface. To open: push cap down while turning. Replace cap after each use. Keep this and all drugs out of reach of children.
TAMPER EVIDENT: For your protection, this bottle has a seal imprinted with the word “Alcon” around the neck. Do not use if seal is damaged or missing at time of purchase.
Store at 20° - 25°C (68° - 77°F). Protect from light.
ALCON LABORATORIES, INC.
FORT WORTH, TX 76134 USA
LOT
EXP:
300035726-0320